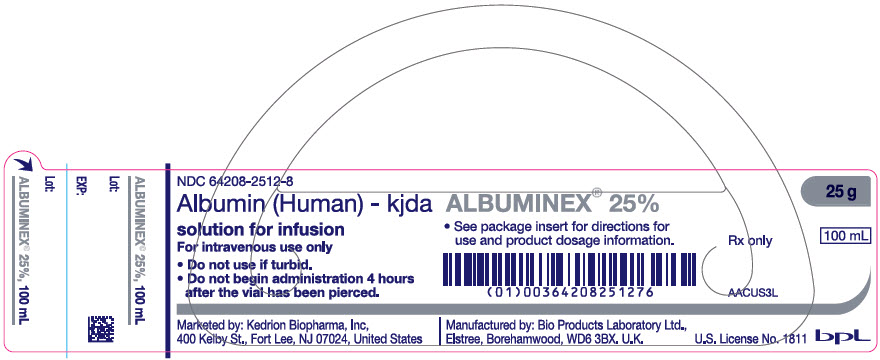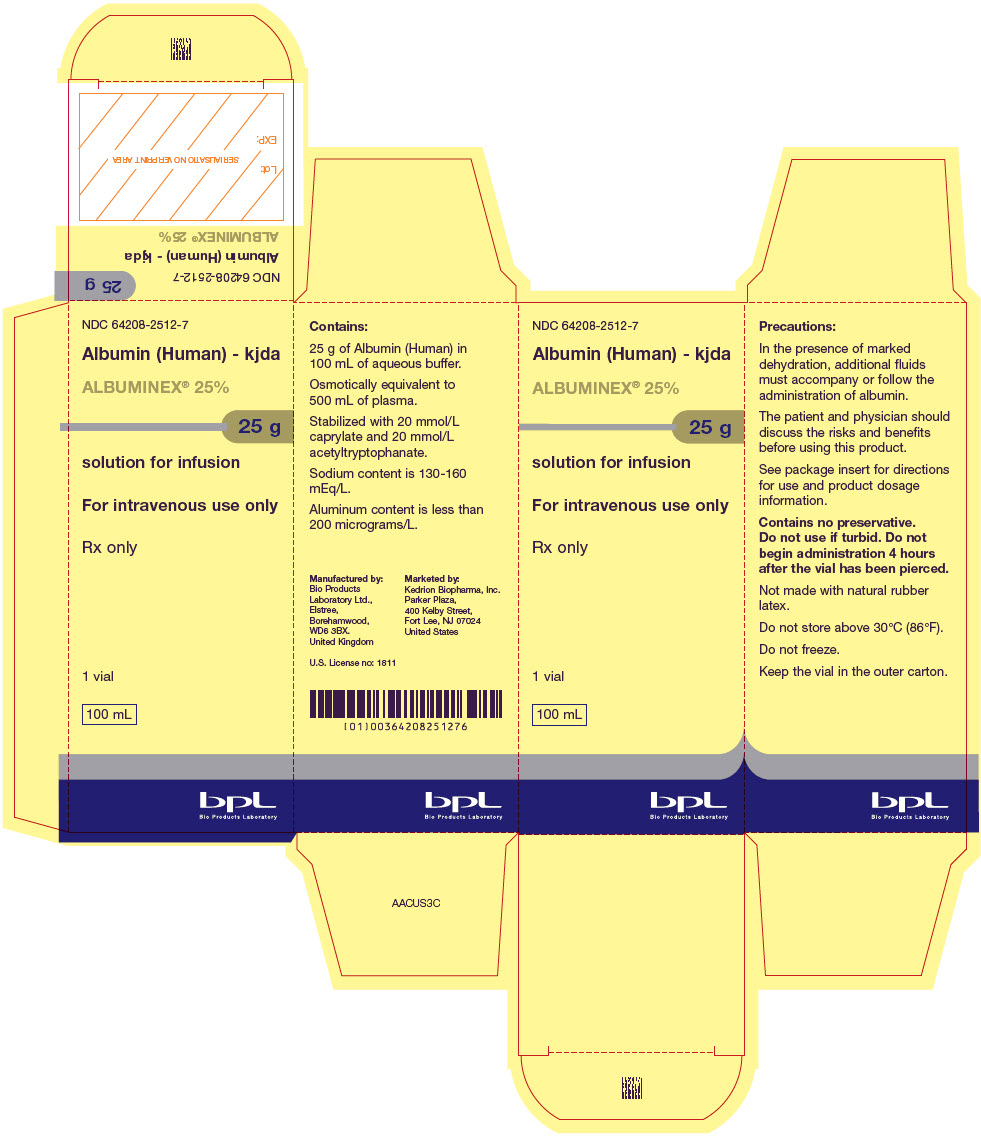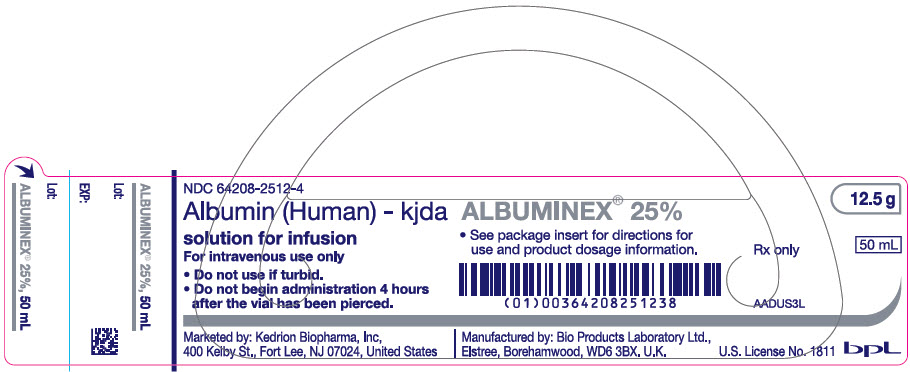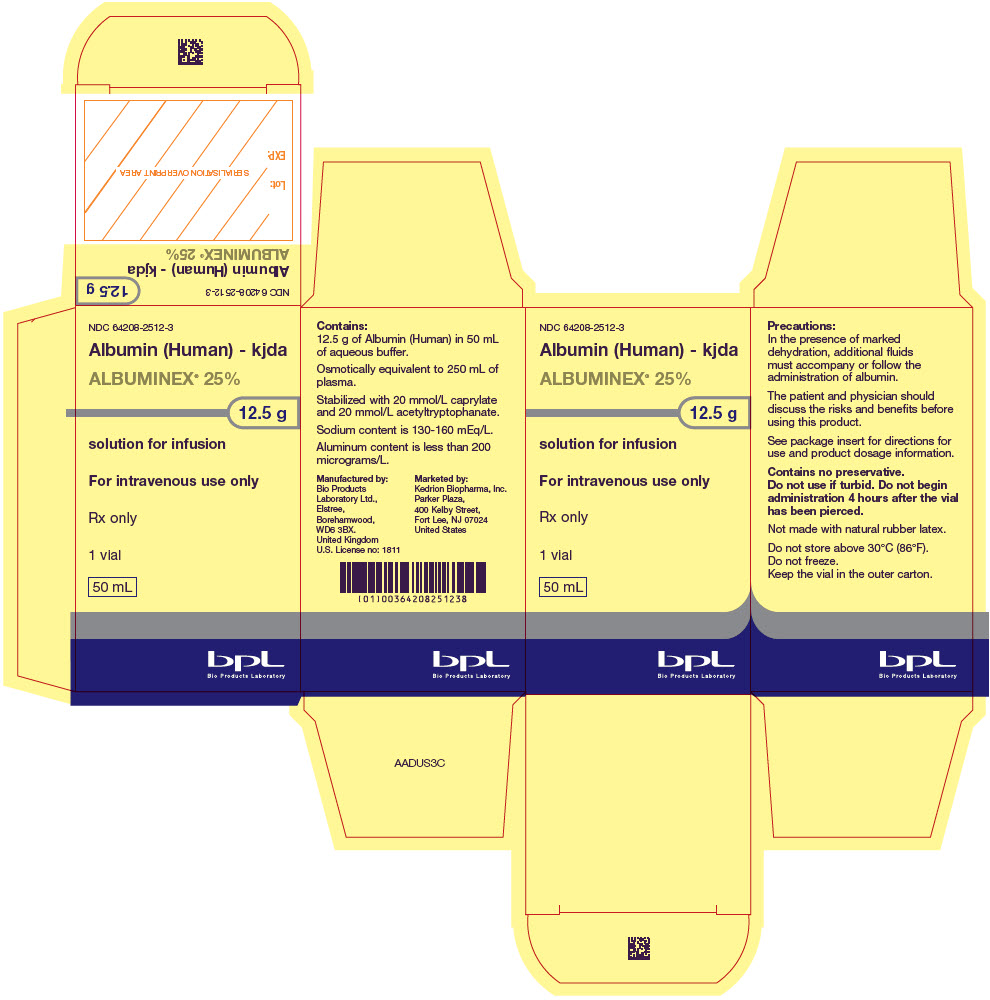 DRUG LABEL: ALBUMINEX
NDC: 64208-2512 | Form: SOLUTION
Manufacturer: BPL
Category: prescription | Type: HUMAN PRESCRIPTION DRUG LABEL
Date: 20241231

ACTIVE INGREDIENTS: Albumin Human 0.25 g/1 mL
INACTIVE INGREDIENTS: Sodium Chloride; Sodium Hydroxide; Caprylic Acid; N-ACETYL-DL-TRYPTOPHAN SODIUM

HIGHLIGHTS OF PRESCRIBING INFORMATION

These highlights do not include all the information needed to use ALBUMINEX® 25% Albumin (human) - kjda safely and effectively. See full prescribing information for ALBUMINEX® 25%.
ALBUMINEX® 25% (human albumin)
solution for injection
Initial U.S. Approval: [2018]

1 INDICATIONS AND USAGE

ALBUMINEX 25% is a 25% albumin solution indicated for adults and children :

- Hypovolemia (1.1)
- Ascites (1.2)
- Hypoalbuminemia including from burns (1.3)
- Acute Nephrosis (1.4)
- Acute Respiratory Distress Syndrome (ARDS) (1.5)
- Cardiopulmonary Bypass (1.6)

2 DOSAGE AND ADMINISTRATION

For intravenous use only.

ALBUMINEX 25% may be diluted with 0.9% saline or 5% dextrose (glucose).

Dosage and infusion rate should be adjusted to the patient's individual requirements.

Indication | Dose
Hypovolemia | Adults: Initial dose of 25 g (including renal dialysis). For acute liver failure: initial dose of 12 to 25 g. (2.1)
Prevention of central volume depletion after paracentesis due to cirrhotic ascites | Adults: 8 g for every 1000 mL of ascitic fluid removed. (2.1)
Hypoalbuminemia including from burns | Adults: 50 to 75 g For pre- and post-operative hypoproteinemia: 50 to 75 g. For burn therapy after the first 24 h: initial dose of 25 g and dose adjustment to maintain plasma protein concentration of 2.5 g per 100 mL. Third space protein loss due to infection: initial dose of 50 to 100 g. (2.1)
Acute nephrosis | Adults: 25 g together with diuretic once a day for 7-10 days. (2.1)
Adult respiratory distress syndrome (ARDS) | Adults: 25 g over 30 minutes and repeated at 8 hours for 3 days, if necessary. (2.1)
Cardiopulmonary bypass procedures | Adults: Initial dose of 25 g. (2.1)

3 DOSAGE FORMS AND STRENGTHS

ALBUMINEX 25% is a solution for infusion:

- ALBUMINEX 25% contains 25 g per dL of human albumin 50 mL (12.5 g) and 100 mL (25 g) glass vials

4 CONTRAINDICATIONS

- Hypersensitivity to human albumin or the excipients
- Severe anemia or cardiac failure with normal or increased intravascular volume

5 WARNINGS AND PRECAUTIONS

- Suspicion of allergic or anaphylactic reactions requires immediate discontinuation of the injection and implementation of appropriate medical treatment. (5.1)
- Hypervolemia may occur if the dosage and rate of infusion are not adjusted to the patient's volume status. Use with caution in conditions where hypervolemia and its consequences or hemodilution could represent a special risk to the patient. (5.2)
- When concentrated albumin is administered, care must be taken to assure adequate hydration of the patient. (5.3)
- Assessment of electrolytes, coagulation and hematology parameters, and hemodynamic status when albumin is administered. (5.4)
- Do not dilute with sterile water for injection. (5.5)
- This product is made from human plasma and may contain infectious agents, e.g., viruses and, theoretically, the Creutzfeldt-Jakob disease agent. (5.6)

6 ADVERSE REACTIONS

The most common adverse reactions are rigors, hypotension/decreased BP, tachycardia/increased heart rate, pyrexia, feeling cold (chills), nausea, vomiting, dyspnea/bronchospasm, rash/pruritus.

Stop the infusion if anaphylaxis, with or without shock, is observed.

To report SUSPECTED ADVERSE REACTIONS, contact Kedrion Biopharma, Inc. at 1-855-3KDRION (1-855-353-7466) or the FDA at 1-800-FDA-1088 or www.fda.gov/medwatch.

FULL PRESCRIBING INFORMATION

1 INDICATIONS AND USAGE

1.1 Hypovolemia

ALBUMINEX 25% is indicated for restoration and maintenance of circulating blood volume where volume deficiency has been demonstrated, and use of a colloid is appropriate e.g. hypovolemia following shock due to trauma or sepsis, in surgical patients and in other similar conditions with volume deficiency when restoration and maintenance of circulating blood volume is required in both adult and pediatric patients. In pediatric patients to reverse hypovolemia and achieve normal capillary refill time.^(1, 2, 3, 4, 5, 6, 7, 8)

1.2 Ascites

ALBUMINEX 25% is indicated for prevention of central volume depletion and maintenance of cardiovascular function after large volume parencentesis in patients with liver cirrhosis or other chronic liver disease in adults and children.^(9, 10, 11, 12)

ALBUMINEX 25% infusion plus administration of vasoactive drugs is indicated in the treatment of type I hepatorenal syndrome.^6

For patients with spontaneous bacterial peritonitis ALBUMINEX 25% is indicated as adjuvant treatment to antibiotic therapy.^(9, 10, 13)

1.3 Hypoalbuminemia Including from Burns

ALBUMINEX 25% is indicated in patients with severe burn injury (> 20% total body surface area), but not until at least 12 to 24 hours after the burn, in order to correct protein loss, decrease overall fluid requirements, decrease systemic edema and stabilize cardiovascular hemodynamics without fluid overload (initial resuscitation should be with crystalloids).^(8, 14)ALBUMINEX 25% is also indicated in patients with pre- or post-operative hypoproteinemia and for third space protein loss due to infection or burns.

1.4 Acute Nephrosis

ALBUMINEX 25% is indicated in patients with acute nephrosis in combination with loop diuretics to reinforce the diuretic therapeutic effect, which is reduced by hypoalbuminemia, and for the correction of reduced oncotic pressure.^(15, 16)

1.5 Acute Respiratory Distress Syndrome (ARDS)

ALBUMINEX 25% is indicated in conjunction with diuretics to correct fluid volume overload associated with ARDS.^(17, 18, 19)

1.6 Cardiopulmonary Bypass

ALBUMINEX 25% is indicated in cardiopulmonary bypass procedures as part of the priming fluids to passivate the synthetic surfaces of the extracorporeal circuit and maintain the patient's colloid oncotic pressure.^(20, 21, 22, 23, 24, 25)

2 DOSAGE AND ADMINISTRATION

For intravenous administration only.

2.1 Dose

The concentration of ALBUMINEX 25% used, its dosage, and infusion rate should be adjusted to the patient's individual requirements and clinical indication.

Indication | Dose
Hypovolemia | Hypovolemia Adults: Initial dose of 25 g. If hemodynamic stability is not achieved within 15 to 30 minutes, an additional dose may be given. For acute liver failure: initial dose of 12 to 25 g. An infusion rate of 1-2 mL per minute is usually indicated. For renal dialysis; the initial dose should not exceed 25 g and patients should be carefully observed for signs of fluid overload.
Prevention of central volume depletion after paracentesis due to cirrhotic ascites | Adults: 8 g for every 1000 mL of ascitic fluid removed.
Hypoalbuminemia including from burns | Adults: 50 to 75 g For pre- and post-operative hypoproteinemia: 50 to 75 g. In burns, therapy usually starts with administration of large volumes of crystalloid solution to maintain plasma volume. After 24 hours: initial dose of 25 g and dose adjustment to maintain plasma protein concentration of 2.5 g per 100 mL or a serum protein concentration of 5.2 g per 100 mL. Third space protein loss due to infection or burns: initial dose of 50 to 100 g. An infusion rate of 1-2 mL per minute is usually indicated in the absence of shock. Treatment should always be guided by hemodynamic response.
Acute nephrosis | Adults: 25 g together with diuretic once a day for 7-10 days
Adult respiratory distress syndrome (ARDS) | Adults: 25 g over 30 minutes and repeated at 8 hours for 3 days, if necessary.
Cardiopulmonary bypass procedures | Adults: Initial dose of 25 g. Additional amounts may be administered as clinically indicated.

2.3 Administration

- Visually inspect the solution for particulate matter and discoloration prior to administration, whenever solution and container permit.
- Do not use if there are any particulates seen or if the solution is discolored.
- If a large volume is infused, ensure that the vial is at room temperature before infusion.
- Do not dilute with Sterile Water for Injection as hemolysis may occur. ALBUMINEX 25% may be diluted with 0.9% saline or 5% dextrose.
- Begin the infusion within 4 hours of piercing the vial stopper (the product does not contain any preservative).
- Adjust the rate of infusion according to the individual patient's hemodynamic and other physiological responses, using appropriate clinical monitoring.

3 DOSAGE FORMS AND STRENGTHS

ALBUMINEX 25% is a sterile, aqueous solution of human albumin (25% w/v i.e. 25 g/dL) for intravenous administration available as:

- 50 mL (12.5 g) single dose vial
- 100 mL (25 g) single dose vial

4 CONTRAINDICATIONS

ALBUMINEX 25% is contraindicated in patients with:

- Hypersensitivity to human albumin or any of the excipients
- Severe anemia or cardiac failure with normal or increased intravascular volume

5 WARNINGS AND PRECAUTIONS

5.1 Hypersensitivity Reactions

Suspicion of allergic or anaphylactic reactions requires immediate discontinuation of the infusion and implementation of appropriate medical treatment.

5.2 Hypervolemia

Hypervolemia may occur if the dosage and rate of infusion are not adjusted to the patient's volume status. At the first clinical signs of cardiovascular overload (headache, dyspnea, jugular venous distention, increased blood pressure), the infusion must be slowed or stopped immediately.

Use albumin with caution in conditions where hypervolemia and its consequences or hemodilution could represent a special risk to the patient. Examples of such conditions are:

- Decompensated heart failure
- Hypertension
- Esophageal varices
- Pulmonary edema
- Hemorrhagic diathesis
- Severe anemia
- Renal and post-renal anuria

5.3 Laboratory Parameters

20% - 25% human albumin solutions are relatively low in electrolytes compared to 4% - 5% human albumin solutions so if comparatively large volumes are to be replaced, care must be taken to ensure adequate substitution of other blood constituents (coagulation factors, electrolytes, platelets and erythrocytes).

5.4 Clinical Hemodynamics Parameters

Colloid-osmotic effect of human albumin 25% is approximately five times that of blood plasma. Therefore, when concentrated albumin is administered, care must be taken to assure adequate hydration of the patient. Patients should be monitored carefully to guard against circulatory overload and hyperhydration. Patients with marked dehydration require administration of additional fluids.

The following parameters should be assessed during administration of ALBUMINEX 25%:

- Arterial blood pressure and pulse rate
- Central venous pressure
- Pulmonary artery occlusion pressure
- Urine output
- Electrolytes
- Hematocrit/hemoglobin

5.5 Pre-infusion Preparation

ALBUMINEX 25% must not be diluted with sterile water for injection as this may cause hemolysis in recipients. The product can be diluted in an isotonic solution (e.g., 5% dextrose in water or 0.9% sodium chloride) [see Dosage and Administration (2.2)].

5.6 Infectious Diseases

Albumin is a derivative of human blood. Based on effective donor screening and product manufacturing processes, it carries an extremely remote risk for transmission of viral diseases. A theoretical risk for transmission of Creutzfeldt-Jakob disease (CJD) is also considered extremely remote. No cases of transmission of viral diseases or CJD have ever been identified for ALBUMINEX 25%.

6 ADVERSE REACTIONS

6.1 General

In general, human albumin solutions are well-tolerated and no specific, clinically relevant alterations in organ function or coagulopathy have been substantiated.^26

The most common adverse reactions associated with infusion of human albumin solutions are rigors, hypotension/decreased BP, tachycardia/increased heart rate, pyrexia, feeling cold (chills), nausea, vomiting, dyspnea/bronchospasm, rash/pruritus. Reactions usually resolve when the infusion is slowed or stopped.

Anaphylaxis, with or without shock, may occur and in this situation, stop the infusion.

6.2 Clinical Trials Experience

No clinical studies were done using ALBUMINEX 25%.

7 DRUG INTERACTIONS

Do not mix ALBUMINEX 25% with blood, blood components, protein hydrolysates, alcoholic solutions or other medicinal products except 0.9% saline or 5% dextrose. However, it can be administered, via a separate IV line, concomitantly with other parenterals.

8 USE IN SPECIFIC POPULATIONS

8.1 Pregnancy

Risk Summary

There are no data with ALBUMINEX 25% use in pregnant women to inform on drug-associated risk. Animal reproduction studies have not been conducted using ALBUMINEX 25%. It is not known whether ALBUMINEX 25% can cause fetal harm when administered to a pregnant woman or can affect fertility. ALBUMINEX 25% should be given to a pregnant woman only if clearly needed. In the U.S. general population, the estimated background risk of major birth defects and miscarriage in clinically recognized pregnancies is 2-4% and 15-20%, respectively.

8.2 Lactation

Risk Summary

There is no information regarding the presence of ALBUMINEX 25% in human milk, the effects on the breast-fed infant, or the effects on milk production. The developmental and health benefits of breast-feeding should be considered along with the mother's clinical need for ALBUMINEX 25% and any potential adverse effects on the breast-fed infant from ALBUMINEX 25% or from the underlying maternal condition.

8.4 Pediatric Use

No human or animal data. Use only if clearly needed.

8.5 Geriatric Use

No human or animal data. Use only if clearly needed.

11 DESCRIPTION

ALBUMINEX 25% is a sterile, ready-for-use, clear, slightly viscous, almost colorless, yellow, amber or slightly green aqueous solution of human albumin for single dose intravenous infusion. It is prepared from the pooled plasma of US donors in FDA-licensed facilities in the US. The product also contains 130-160 mmol/L of sodium, less than 200 micrograms/L of aluminum and is stabilized with caprylate (0.08 mmol/g albumin) and acetyltryptophanate (0.08 mmol/g albumin) but does not contain any preservative.

12.5 g (50 mL) of ALBUMINEX 25% is oncotically equivalent to 250 mL plasma.
25 g (100 mL) of ALBUMINEX 25% is oncotically equivalent to 500 mL plasma.

The vials are closed with a synthetic rubber stopper. The stopper is not made with natural rubber latex.

The viral risk from human plasma is minimized by the fractionation process and pasteurization of the albumin solution for 10 hours at 60°C (140°F) in its final container. These processes are effective for both enveloped and non-enveloped viruses. There have been no reports of virus transmission with products manufactured using this combination of processes. Typical reductions of experimental viral loads are shown in Table 1.

Table 1: Virus Reduction for Albumin (Human) 25%
Mean Reduction Factors (log10)
 | Enveloped Virus | Enveloped Virus | Enveloped Virus | Enveloped Virus | Non-Enveloped Virus | Non-Enveloped Virus
Manufacturing Step | HIV-1 | Sindbis | BVDV | IBR | HAV | CPV
A+1 Precipitation | nd | 4.1 | >3.4 | 3.4 | 3.4 | 3.7
Fraction IV Precipitation | >4.6 | >7.1 | >4.2 | >5.7 | 4.2 | 6.0
Pasteurization | >6.6 | >6.2 | >4.0 | >5.0 | 4.7 | 4.2
Overall | >11.2 | >13.3 | >8.2 | >10.7 | 8.9 | 10.2
nd: not determined
HIV-1: Human Immunodeficiency Virus Type 1
BVDV: Bovine Viral Diarrhoea Virus
IBR: Infectious Bovine Rhinotracheitis
HAV: Hepatitis A Virus
CPV: Canine Parvovirus

12 CLINICAL PHARMACOLOGY

12.1 Mechanism of Action

Human albumin accounts for more than half of the total protein in the plasma and represents about 10% of protein synthesis activity by the liver. Human Albumin 25% has a corresponding hyperoncotic effect.

The primary physiological function of albumin results from its contribution to plasma colloid oncotic pressure and transport function. Albumin stabilizes circulating blood volume and is a carrier of hormones, enzymes, medicinal products and toxins. Other physiological functions include antioxidant properties, free radical scavenging, and capillary membrane integrity.

12.3 Pharmacokinetics

Albumin is distributed throughout the extracellular space and more than 60% of the body albumin pool is located in the extravascular fluid compartment. Albumin has a circulating life span of 15-20 days, with a turnover of approximately 15 g per day.

The balance between synthesis and breakdown is normally achieved by feedback regulation. Elimination is predominantly intracellular and due to lysosome proteases.

In healthy subjects, less than 10% of infused albumin leaves the intravascular compartment during the first 2 hours following infusion. There is considerable individual variation in the effect of albumin on plasma volume.

In some patients, the plasma volume can remain elevated for several hours. In critically ill patients, however, albumin can leak out of the vascular space in substantial amounts at an unpredictable rate.

15 REFERENCES

1. Finfer S, Bellomo R, Boyce N, et al. A comparison of albumin and saline for fluid resuscitation in the intensive care unit. N Engl J Med 2004;3650:2247-2256
2. Bunn F, Trivedi D, Ashraf S. Colloid solutions for fluid resuscitation. Cochrane Database of Systematic Reviews 2011, Issue 3. Art. No.: CD001319. DOI: 10.1002/14651858.CD001319.pub3
3. Powell-Tuck J, Gosling P, Lobo DN, et al. British Consensus Guidelines on Intravenous Fluid Therapy for Adult Surgical Patients. BAPEN; 2011. Available from: http://www.bapen.org.uk/pdfs/bapen_pubs/giftasup.pdf (Guideline Ref ID GIFTASUP2011)
4. Rochwerg B, Alhazzani W, Sindi A, et al. Fluid resuscitation in sepsis: a systematic review and network meta-analysis. Ann Intern Med 2014;161(5):347-355
5. Wiedermann CJ, Joannidis M. Albumin replacement in severe sepsis or septic shock. N Engl J Med 2014;371:83-84
6. Akech S, Gwer S, Idro R, et al. Volume expansion with albumin compared to gelofusine in children with severe malaria: results of a controlled trial. PLoS Clin Trials 2006; 5:0001-0011
7. Dellinger RP, Levy MM, Rhodes A, et al. Surviving sepsis campaign: international guidelines for management of severe sepsis and septic shock: 2012. Critical Care Medicine, 2013; 41(2):580–637
8. Perel P, Roberts I, Ker K. Colloids versus crystalloids for fluid resuscitation in critically ill patients. Cochrane Database of Systemic Reviews 2013, Issue 2.Art. No.CD000567. DOI:10.1002/14651858.CD000567.pub6.
9. Runyon BA. Management of Adult Patients with Ascites Due to Cirrhosis: Update 2012. The American Association for the Study of Liver Diseases 2012. http://www.aasld.org/publications/practice-guidelines-0 [accessed 15 April 2016]
10. EASL clinical practise guidelines on the management of ascites, spontaneous bacterial peritonitis, and hepatorenal syndrome in cirrhosis. J Hepatol 2010; 53: 397–417
11. Bernardi M, Carceni P, Navickis RJ, et al. Albumin infusion in patients undergoing large-volume paracentesis: a meta-analysis of randomized trials. Hepatology 2012;55:1172-1181
12. Sarma MS, Yachha SK, Bhatia V, et al. Safety, complications and outcome of large volume paracentesis with or without albumin therapy in children with severe ascites due to liver disease. J Hepatol 2015:63;1126-1132
13. Wiest R, Krag A, Gerbes A. Spontaneous Bacterial Peritonitis. Recent Guidelines and Beyond. Gut 2012; 61(2):297-310
14. Pham TN, Cancio LC, Gibran NS. American Burn Association Practice Guidelines Burn Shock Resuscitation. J Burn Care Res 2008; 29(1): 257-266
15. Bircan Z, Kervancioglu M. Does albumin and furosemide therapy affect plasma volume in nephrotic children? Pediatr Nephrol 2001;16:497-499
16. Dharmaraj R, Hari P, Bagga A, Randomized cross-over trial comparing albumin and frusemide infusions in nephrotic syndrome. Pediatr Nephrol 2009; 24(4):775-782
17. Martin GS, Moss M, Wheeler AP, et al. A randomized, controlled trial of furosemide with or without albumin in hypoproteinemic patients with acute lung injury. Crit Care Med 2005;33(8):1681-1687
18. Uhlig C, Pedro L, Silva PL, et al. Albumin versus crystalloid solutions in patients with the acute respiratory distress syndrome: a systematic review and meta-analysis. Crit Care 2014, 18:R10 http://ccforum.com/content/18/1/R10 [accessed 02 November 2016]
19. Quinlan GJ, Mumby S, Martin GS, et al. Albumin influences total plasma antioxidant capacity favorably in patients with acute lung injury. Crit Care Med 2004;32:755–759
20. Wilkes MM, Navickis RJ, Sibbald WJ. Albumin versus hydroxyethyl starch in cardiopulmonary bypass surgery: a meta- analysis of postoperative bleeding. Ann Thorac Surg 2001;72(2):527-534
21. Golab HD, Scohy TV, de Jong PL, et al. Relevance of colloid oncotic pressure regulation during neonatal and infant cardiopulmonary bypass: a prospective randomized study. Eur J Cardio-Thor Surg 2011; 39(6):886-891
22. Hanart C, Khalife M, De Villé A, et al. Perioperative volume replacement in children undergoing cardiac surgery: Albumin versus hydroxyethyl starch 130/0.4. Crit Care Med 2009;37 (2): 696-701 DOI: 10.1097/CCM.0b013e3181958c81
23. Loeffelbein F, Zirell U, Benk C, et al. High colloid oncotic pressure priming of cardiopulmonary bypass in neonates and infants: implications on haemofiltration, weight gain and renal function. Eur J Cardio-Thor Surg 2008; 34(3):648-652
24. Oliver WC Jr, Beynen FM, Nuttall GA, et al. Blood loss in infants and children for open heart operations: albumin 5% versus fresh-frozen plasma in the prime. Ann Thor Surg 2003;75(5):1506-1512
25. Yu K, Liu Y, Hei F, et al. Effect of different albumin concentrations in extracorporeal circuit prime on perioperative fluid status in young children. ASAIO Journal 2008; 54(5):463-466
26. German Medical Association. Cross-Sectional Guidelines for Therapy with Blood Components and Plasma Derivatives. 4th revised and updated edition 2014. http://www.bundesaerztekammer.de/aerzte/medizin-ethik/wissenschaftlicher-beirat/veroeffentlichungen/haemotherapie-transfusionsmedizin/english/ [accessed 15 April 2016]

16 HOW SUPPLIED/STORAGE AND HANDLING

How ALBUMINEX 25% is supplied

ALBUMINEX 25%, 25 g/dL in clear Type II glass vials.

Strength | Grams and fill size | NDC carton number | NDC vial number
25% | 12.5 g in 50 mL | 64208-2512-3 | 64208-2512-4
25% | 25 g in 100 mL | 64208-2512-7 | 64208-2512-8

Not all pack sizes may be marketed.

Storage and handling

Do not store above 30°C (86°F).

Keep the vial stored in the outer carton in order to protect from light.

Do not freeze.

Do not use ALBUMINEX 25% after the expiration date which is stated on the carton and label after "EXP." The expiration date refers to the last day of that month.

ALBUMINEX 25% should be inspected visually for particulate matter and discoloration prior to administration.

U.S. federal law prohibits dispensing without prescription.

17 PATIENT COUNSELING INFORMATION

Ensure that patients to be treated with ALBUMINEX 25% are informed of the potential risks and benefits of its use for their clinical condition [see Warnings and Precautions (5)].

Check that they are not known to be allergic to the product or its excipients [see Contraindications (4) and Description (11)].

Make them aware of the symptoms of anaphylaxis [see Hypersensitivity (5.1)].

Make them aware of the symptoms of potential circulatory overload [see Hypervolemia (5.2)

Inform patients that because ALBUMINEX 25% is derived from human blood plasma it may contain infectious agents that cause disease (e.g. viruses and, theoretically CJD agent) although the risk of infection from ALBUMINEX 25% has been reduced by the procedures used in donor selection and during manufacture [see Infectious Diseases (5.6) and Description (11)].

Manufactured by:
Bio Products Laboratory Ltd.,
Elstree,
Borehamwood,
WD6 3BX.
United Kingdom

Marketed by:
Kedrion Biopharma, Inc.
Parker Plaza,
400 Kelby Street,
Fort Lee, NJ 07024
United States

U.S. Licence No: 1811

ALBUMINEX® is a registered trademark of Bio Products Laboratory Ltd.

Version 2

PRINCIPAL DISPLAY PANEL - 100 mL Vial Label

NDC 64208-2512-8

Albumin (Human) - kjda

solution for infusion
For intravenous use only

- Do not use if turbid.
- Do not begin administration 4 hours
  after the vial has been pierced.

Marketed by: Kedrion Biopharma, Inc,
400 Kelby St., Fort Lee, NJ 07024, United States

PRINCIPAL DISPLAY PANEL - 100 mL Vial Carton

NDC 64208-2512-7

Albumin (Human) - kjda

ALBUMINEX® 25%

25 g

solution for infusion

For intravenous use only

Rx only

1 vial

100 mL

Bio Products Laboratory

PRINCIPAL DISPLAY PANEL - 50 mL Vial Label

NDC 64208-2512-4

Albumin (Human) - kjda

solution for infusion
For intravenous use only

- Do not use if turbid.
- Do not begin administration 4 hours
  after the vial has been pierced.

Marketed by: Kedrion Biopharma, Inc,
400 Kelby St., Fort Lee, NJ 07024, United States

PRINCIPAL DISPLAY PANEL - 50 mL Vial Carton

NDC 64208-2512-3

Albumin (Human) - kjda

ALBUMINEX® 25%

12.5 g

solution for infusion

For intravenous use only

Rx only

1 vial

50 mL

Bio Products Laboratory